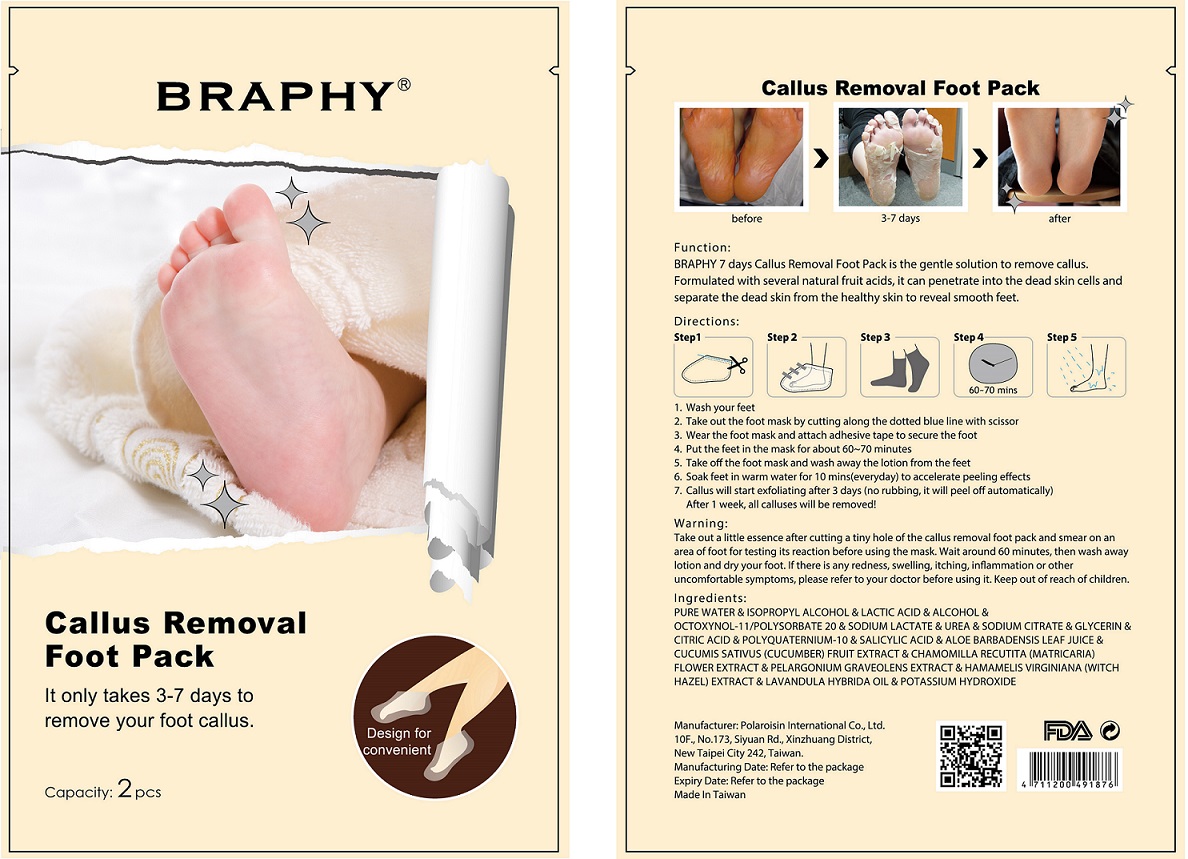 DRUG LABEL: Callus Removal Foot Pack
NDC: 69264-016 | Form: PATCH
Manufacturer: POLAROISIN INTERNATIONAL CO., LTD.
Category: otc | Type: HUMAN OTC DRUG LABEL
Date: 20151217

ACTIVE INGREDIENTS: SALICYLIC ACID 11.9 mg/2 1
INACTIVE INGREDIENTS: WATER; ISOPROPYL ALCOHOL; LACTIC ACID, UNSPECIFIED FORM; ALCOHOL; OCTOXYNOL-11; POLYSORBATE 20; SODIUM LACTATE; UREA; SODIUM CITRATE; GLYCERIN; CITRIC ACID MONOHYDRATE; POLYQUATERNIUM-10 (1000 MPA.S AT 2%); ALOE VERA LEAF; CUCUMBER; CHAMOMILE; PELARGONIUM GRAVEOLENS FLOWERING TOP; HAMAMELIS VIRGINIANA TOP; LAVANDIN OIL; POTASSIUM HYDROXIDE

Callus Removal Foot Pack

ACTIVE INGREDIENT

Salicylic acid 11.9 mg/One pair

PURPOSE

Remove callus

Keep out of reach of children

Function:

BRAPHY 7 days Callus Removal Foot Pack is the gentle solution to remove callus. Formulated with several natural fruit acids, it can penetrate into the dead skin cells and separate the dead skin from the healthy skin to reveal smooth feet

Warning:

Take out a little essence after cutting a tiny hole of the callus removal foot pack and smear on an area of foot for testing its reaction before using the mask. Wait around 60 minutes, then wash away lotion and dry your foot. If there is any redness, swelling, itching, inflammation or other uncomfortable symptoms, please refer to your doctor before using it.

Directions:

1. Wash your feet
2. Take out the foot mask by cutting along the dotted blue line with scissor
3. Wear the foot mask and attach adhesive tape to secure the foot
4. Put the feet in the mask for about 60-70 minutes
5. Take off the foot mask and wash away the lotion from the feet
6. Soak feet in warm water for 10 mins(everyday) to accelerate peeling effects
7. Callus will start exfoliating after 3 days (no rubbing, it will peel off automatically). After 1 week, all calluses will be removed!

Ingredients:

PURE WATER & ISOPROPYL ALCOHOL & LACTIC ACID & ALCOHOL & OCTOXYNOL-11/POLYSORBATE 20 & SODIUM LACTATE & UREA & SODIUM CITRATE & GLYCERIN & CITRIC ACID & POLYQUATERNIUM-10 & SALICYLIC ACID & ALOE BARBADENSIS LEAF JUICE & CUCUMIS SATIVUS (CUCUMBER) FRUIT EXTRACT & CHAMOMILLA RECUTITA (MATRICARIA) FLOWER EXTRACT & PELARGONIUM GRAVEOLENS EXTRACT & HAMAMELIS VIRGINIANA (WITCH HAZEL) EXTRACT & LAVANDULA HYBRIDA OIL & POTASSIUM HYDROXIDE

Design for convenient

Manufacturer: Polaroisin International Co.,Ltd.

10F., No.173, Siyuan Rd., Xinzhuang District,

New Taipei City 242, Taiwan.

Made In Taiwan